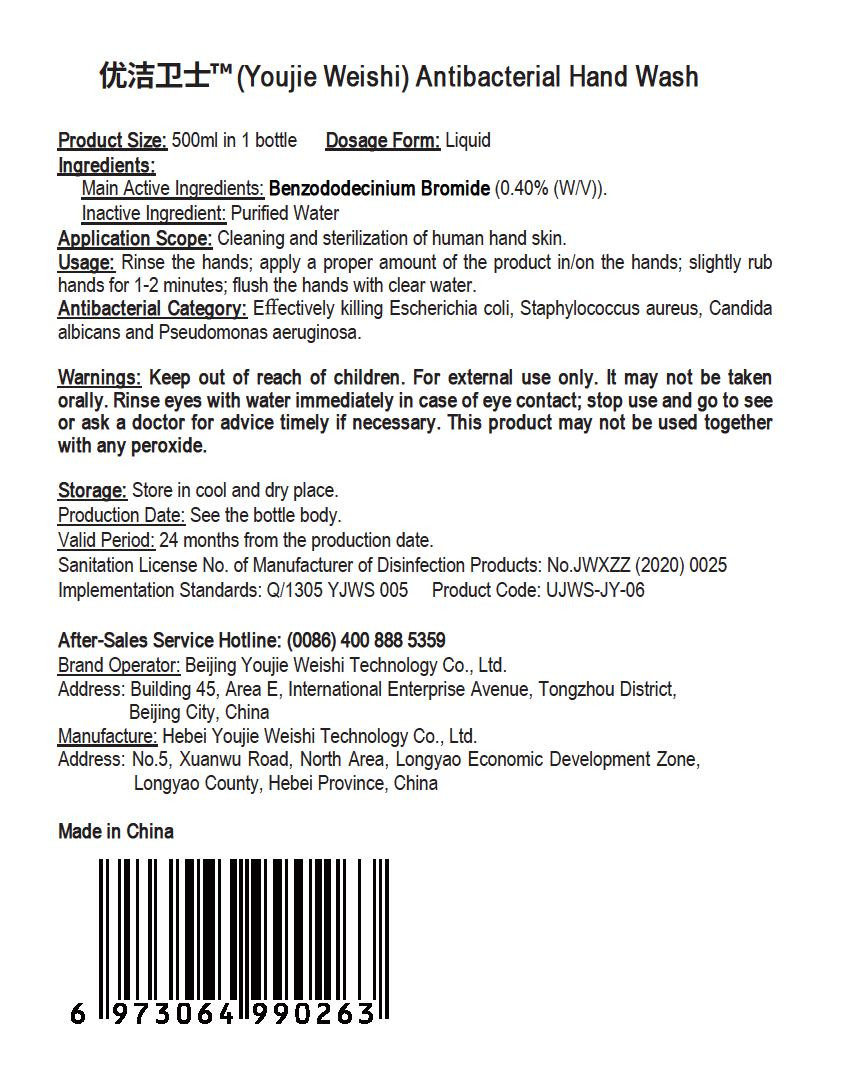 DRUG LABEL: Youjie Weishi Antibacterial Hand Wash
NDC: 55455-006 | Form: LIQUID
Manufacturer: Hebei Youjie Weishi Technology Co., Ltd.
Category: otc | Type: HUMAN OTC DRUG LABEL
Date: 20200507

ACTIVE INGREDIENTS: BENZODODECINIUM BROMIDE 2 g/500 mL
INACTIVE INGREDIENTS: WATER

PURPOSE

Disinfection
Sterilization
No Rinseing

INACTIVE INGREDIENT

water

DOSAGE AND ADMINISTRATION

Store in cool and dry place.

ACTIVE INGREDIENT

Benzalkonium Bromide

keep out of reach of children

INDICATIONS AND USAGE

Rinse the hands; apply a proper amount of the product in/on the hands; slightly rub hands for 1-2 minutes; flush the hands with clear water.

Keep out of reach of children. For external use only. It may not be taken orally. Rinse eyes with water immediately in case of eye contact; stop use and go to see or ask a doctor for advice timely if necessary. This product may not be used together with any peroxide.